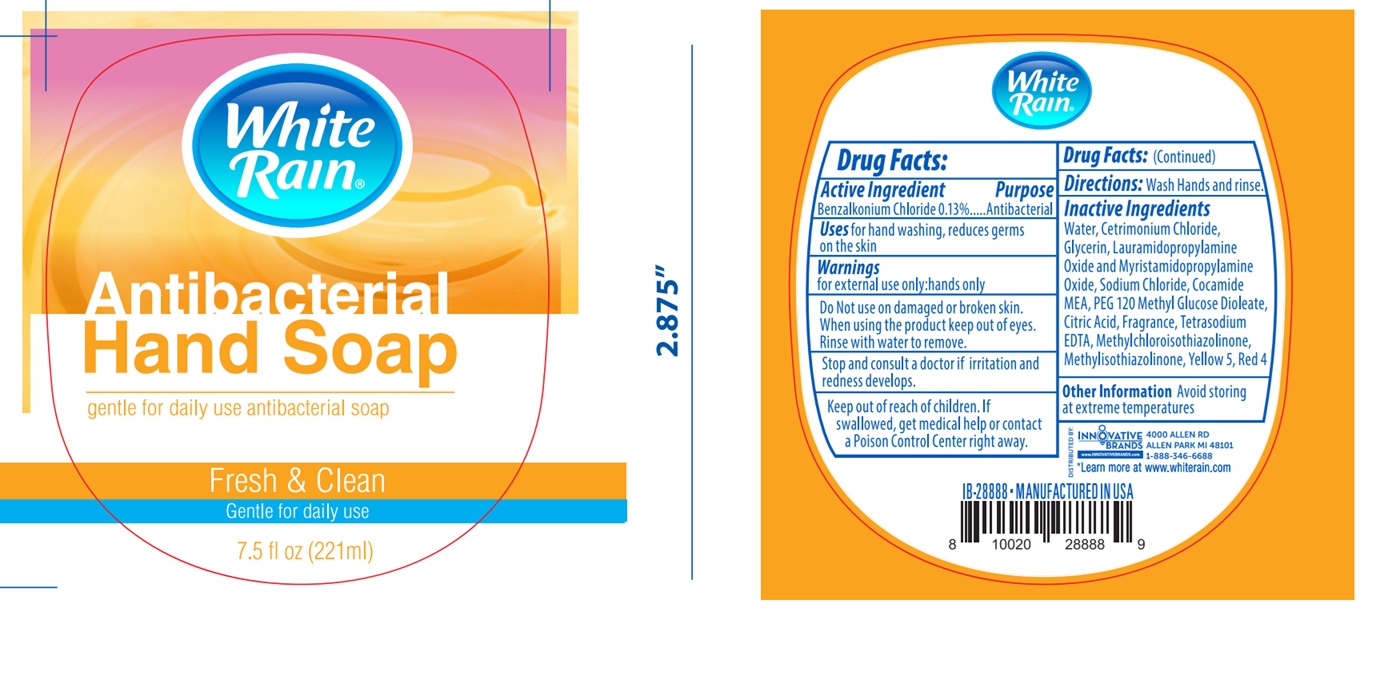 DRUG LABEL: White Rain Antibacterial Hand Fresh and Clean
NDC: 52862-627 | Form: SOAP
Manufacturer: International Wholesale, Inc.
Category: otc | Type: HUMAN OTC DRUG LABEL
Date: 20250528

ACTIVE INGREDIENTS: BENZALKONIUM CHLORIDE 1.3 mg/1 mL
INACTIVE INGREDIENTS: TETRASODIUM EDTA; WATER; CETRIMONIUM CHLORIDE; GLYCERIN; LAURAMIDOPROPYLAMINE OXIDE; MYRISTAMIDOPROPYLAMINE OXIDE; SODIUM CHLORIDE; COCO MONOETHANOLAMIDE; PEG-120 METHYL GLUCOSE DIOLEATE; CITRIC ACID MONOHYDRATE; METHYLCHLOROISOTHIAZOLINONE; METHYLISOTHIAZOLINONE; FD&C YELLOW NO. 5; FD&C RED NO. 4

White Rain Antibacterial Hand Soap, Fresh and Clean

Active Ingredient

Benzalkonium Chloride 0.13%

Purpose

Antibacterial

Uses

for hand washing, reduces germs on the skin

Warnings

for external use only-hands only.

Do Not use

on damaged or broken skin.

When using the product

keep out of eyes. Rinse with water to remove.

Stop and consult a doctor if

irritation and redness develops.

Keep out of reach of children.

If swallowed, get medical help or contact a Poison Control Center right away.

Directions:

Wash hands and rinse.

Inactive Ingredients

Water, Cetrimonium Chloride, Glycerin, Lauramidopropylamine Oxide and Myristamidopropylamine Oxide, Sodium Chloride, Cocamide MEA, PEG-120 Methyl Glucose Dioleate, Citric Acid, Tetrasodium EDTA, Methylchloroisothiazolinone, Methylisothiazolinone, Yellow 5, Red 4

Other Information

Avoid storing at extreme temperatures.